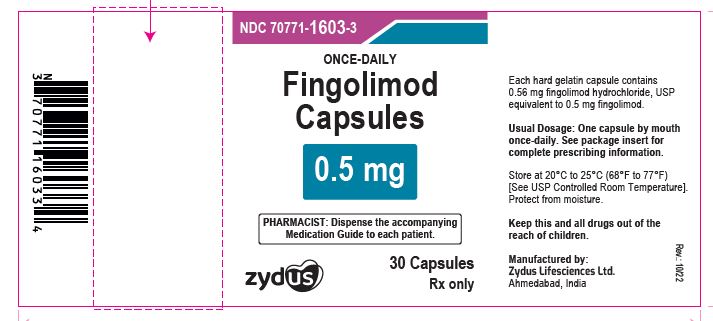 DRUG LABEL: Fingolimod
NDC: 70771-1603 | Form: CAPSULE
Manufacturer: Zydus Lifesciences Limited
Category: prescription | Type: HUMAN PRESCRIPTION DRUG LABEL
Date: 20241130

ACTIVE INGREDIENTS: FINGOLIMOD HYDROCHLORIDE 0.5 mg/1 1
INACTIVE INGREDIENTS: ALCOHOL; AMMONIA; BUTYL ALCOHOL; FERRIC OXIDE YELLOW; FERROSOFERRIC OXIDE; GELATIN; ISOPROPYL ALCOHOL; POTASSIUM HYDROXIDE; PROPYLENE GLYCOL; SHELLAC; SODIUM LAURYL SULFATE; SODIUM STEARYL FUMARATE; STARCH, CORN; TITANIUM DIOXIDE; WATER

Fingolimod Capsules

PACKAGE LABEL.PRINCIPAL DISPLAY PANEL

NDC 70771-1603-3

Fingolimod Capsules, 0.5 mg

30 Capsules

Rx only